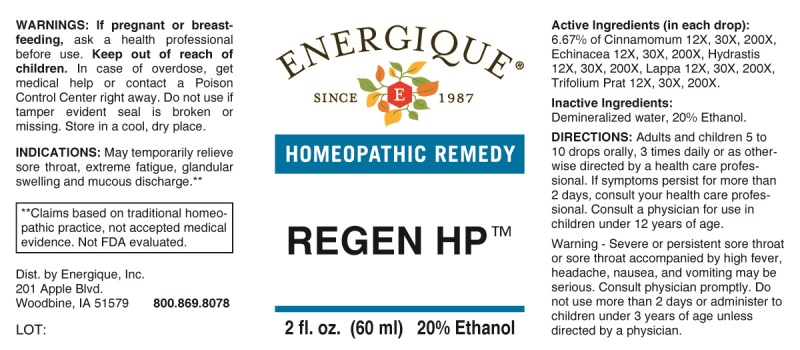 DRUG LABEL: Regen
NDC: 44911-0529 | Form: LIQUID
Manufacturer: Energique, Inc.
Category: homeopathic | Type: HUMAN OTC DRUG LABEL
Date: 20240703

ACTIVE INGREDIENTS: CINNAMON 12 [hp_X]/1 mL; ECHINACEA ANGUSTIFOLIA WHOLE 12 [hp_X]/1 mL; GOLDENSEAL 12 [hp_X]/1 mL; ARCTIUM LAPPA ROOT 12 [hp_X]/1 mL; TRIFOLIUM PRATENSE FLOWER 12 [hp_X]/1 mL
INACTIVE INGREDIENTS: WATER; ALCOHOL

DRUG FACTS:

ACTIVE INGREDIENTS:

(in each drop): 6.67% of Cinnamomum 12X, 30X, 200X, Echinacea (Angustifolia) 12X, 30X, 200X, Hydrastis Canadensis 12X, 30X, 200X, Lappa Major 12X, 30X, 200X, Trifolium Pratense 12X, 30X, 200X.

INDICATIONS:

May temporarily relieve sore throat, extreme fatigue, glandular swelling and mucous discharge.**

**Claims based on traditional homeopathic practice, not accepted medical evidence. Not FDA evaluated.

WARNINGS:

If pregnant or breast-feeding, ask a health professional before use.

Keep out of reach of children. In case of overdose, get medical help or contact a Poison Control Center right away.

Do not use if tamper evident seal is broken or missing. Store in a cool, dry place.

Warning - Severe or persistent sore throat or sore throat accompanied by high fever, headache, nausea, and vomiting may be serious. Consult a physician promptly. Do not use more than 2 days or administer to children under 3 years of age unless directed by a physician.

Keep out of reach of children. In case of overdose, get medical help or contact a Poison Control Center right away.

DIRECTIONS:

Adults and children 5 to 10 drops orally, 3 times daily or as otherwise directed by a health care professional. If symptoms persist for more than 2 days, consult your health care professional. Consult a physician for use in children under 12 years of age.

INDICATIONS:

May temporarily relieve sore throat, extreme fatigue, glandular swelling and mucous discharge.**

**Claims based on traditional homeopathic practice, not accepted medical evidence. Not FDA evaluated.

INACTIVE INGREDIENTS:

Demineralized water, 20% Ethanol.

QUESTIONS:

Dist. by Energique, Inc.

201 Apple Blvd

Woodbine, IA 51579 800-869-8078

PACKAGE LABEL DISPLAY:

ENERGIQUE

SINCE 1987

HOMEOPATHIC REMEDY

REGEN HP

2 fl. oz. (60 ml)